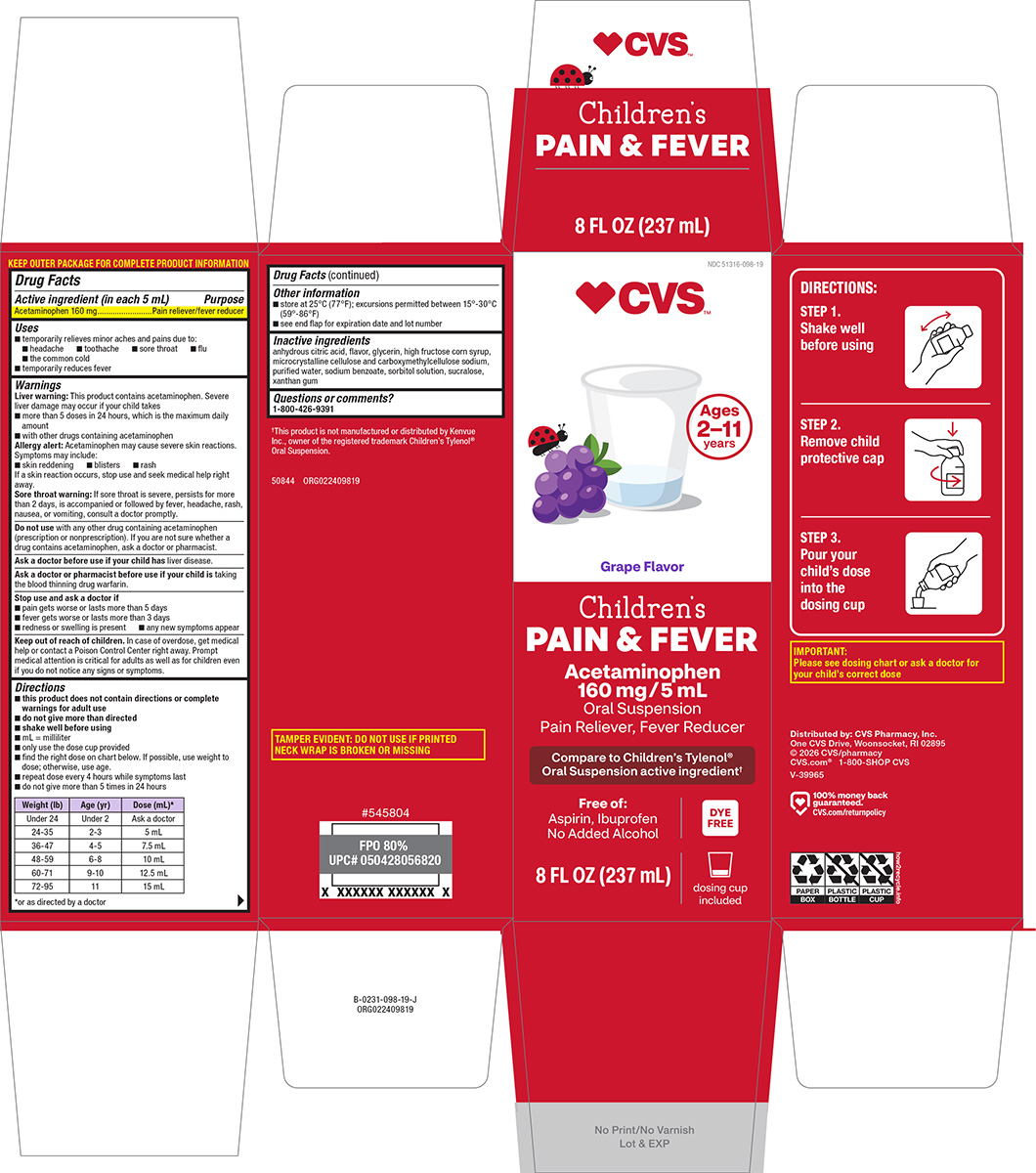 DRUG LABEL: Childrens Pain and Fever
NDC: 51316-098 | Form: SUSPENSION
Manufacturer: CVS WOONSOCKET PRESCRIPTION CENTER, INCORPORATED
Category: otc | Type: HUMAN OTC DRUG LABEL
Date: 20260225

ACTIVE INGREDIENTS: ACETAMINOPHEN 160 mg/5 mL
INACTIVE INGREDIENTS: ANHYDROUS CITRIC ACID; GLYCERIN; HIGH FRUCTOSE CORN SYRUP; MICROCRYSTALLINE CELLULOSE; CARBOXYMETHYLCELLULOSE SODIUM, UNSPECIFIED; WATER; SODIUM BENZOATE; SORBITOL SOLUTION; SUCRALOSE; XANTHAN GUM

CVS 44-098

Active ingredient (in each 5 mL)

Acetaminophen 160 mg

Purpose

Pain reliever/fever reducer

Uses

- temporarily relieves minor aches and pains due to:
  - headache
  - toothache
  - sore throat
  - flu
  - the common cold
- temporarily reduces fever

Warnings

Liver warning: This product contains acetaminophen. Severe liver damage may occur if your child takes

- more than 5 doses in 24 hours, which is the maximum daily amount
- with other drugs containing acetaminophen

Allergy alert: Acetaminophen may cause severe skin reactions. Symptoms may include:

- skin reddening
- blisters
- rash

If a skin reaction occurs, stop use and seek medical help right away.

Sore throat warning: If sore throat is severe, persists for more than 2 days, is accompanied or followed by fever, headache, rash, nausea, or vomiting, consult a doctor promptly.

Do not use

with any other drug containing acetaminophen (prescription or nonprescription). If you are not sure whether a drug contains acetaminophen, ask a doctor or pharmacist.

Ask a doctor before use if your child has

liver disease.

Ask a doctor or pharmacist before use if your child is

taking the blood thinning drug warfarin.

Stop use and ask a doctor if

- pain gets worse or lasts more than 5 days
- fever gets worse or lasts more than 3 days
- redness or swelling is present
- any new symptoms appear

Keep out of reach of children.

In case of overdose, get medical help or contact a Poison Control Center right away. Prompt medical attention is critical for adults as well as for children even if you do not notice any signs or symptoms.

Directions

- this product does not contain directions or complete warnings for adult use
- do not give more than directed
- shake well before using
- mL = milliliter
- only use the dose cup provided
- find the right dose on chart below. If possible, use weight to dose; otherwise, use age.
- repeat dose every 4 hours while symptoms last
- do not give more than 5 times in 24 hours

Weight (lb) | Age (yr) | Dose (mL)*
Under 24 | Under 2 | Ask a doctor
24-35 | 2-3 | 5 mL
36-47 | 4-5 | 7.5 mL
48-59 | 6-8 | 10 mL
60-71 | 9-10 | 12.5 mL
72-95 | 11 | 15 mL

*or as directed by a doctor

Other information

- store at 25°C (77°F); excursions permitted between 15°-30°C (59°-86°F)
- see end flap for expiration date and lot number

Inactive ingredients

anhydrous citric acid, flavor, glycerin, high fructose corn syrup, microcrystalline cellulose and carboxymethylcellulose sodium, purified water, sodium benzoate, sorbitol solution, sucralose, xanthan gum

Questions or comments?

1-800-426-9391

Principal display panel

NDC 51316-098-19

♥︎CVS™

Ages
2–11
years

Grape Flavor

Children’s
PAIN & FEVER

Acetaminophen
160 mg / 5 mL
Oral Suspension
Pain Reliever, Fever Reducer

Compare to Children’s Tylenol®
Oral Suspension active ingredient†

Free of:
Aspirin, Ibuprofen
No Added Alcohol

DYE
FREE

8 FL OZ (237 mL)

dosing cup
included

DIRECTIONS:

Step 1.
Shake well
before using

Step 2.
Remove child
protective cap

Step 3.
Pour your
child’s dose
into the
dosing cup

IMPORTANT:
Please see dosing chart or ask a doctor for
your child’s correct dose

TAMPER EVIDENT: DO NOT USE IF PRINTED
NECK WRAP IS BROKEN OR MISSING

†This product is not manufactured or distributed by Kenvue
Inc., owner of the registered trademark Children’s Tylenol®
Oral Suspension.

50844 ORG022409819

Distributed by: CVS Pharmacy, Inc.
One CVS Drive, Woonsocket, RI 02895
© 2026 CVS/pharmacy
CVS.com® 1-800-SHOP CVS
V-39965

♥︎ 100% money back
guaranteed.
CVS.com/returnpolicy

CVS 44-098